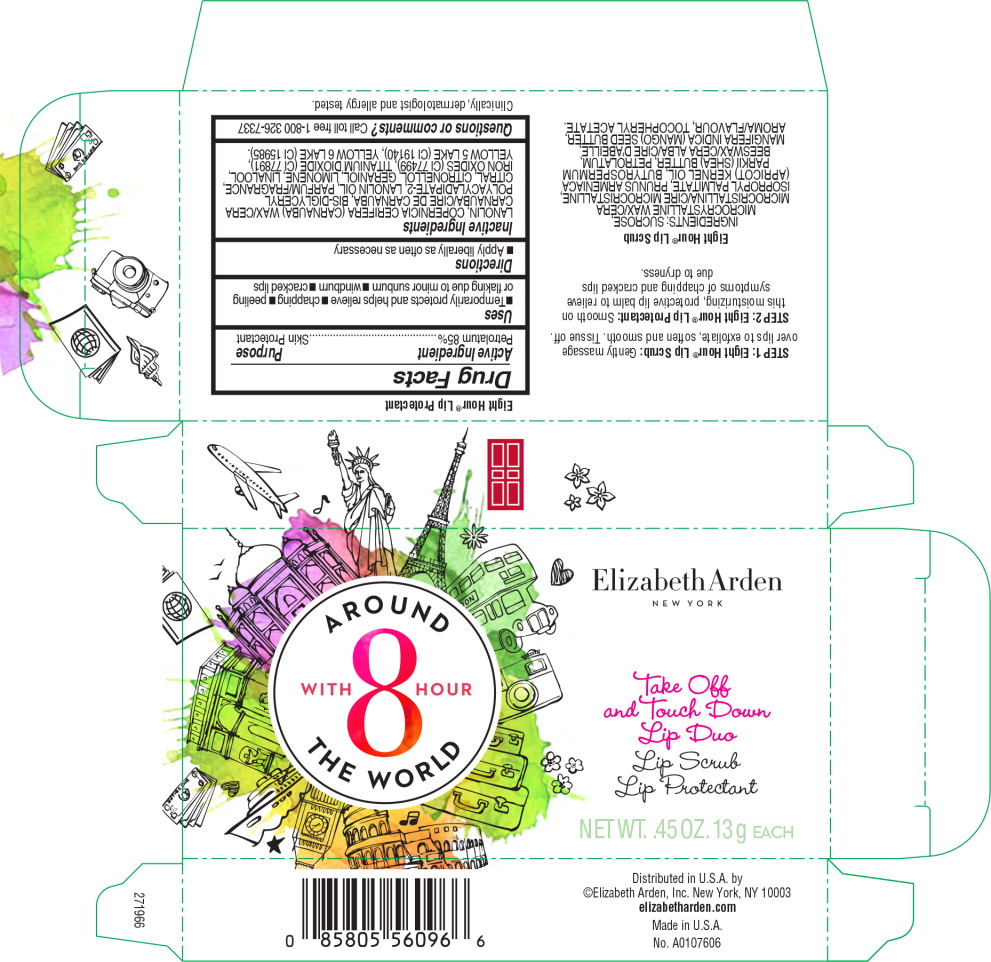 DRUG LABEL: ELIZABETH ARDEN EIGHT HOUR LIP PROTECTANT
NDC: 67938-3052 | Form: GEL
Manufacturer: ELIZABETH ARDEN, INC
Category: otc | Type: HUMAN OTC DRUG LABEL
Date: 20170801

ACTIVE INGREDIENTS: PETROLATUM 1 g/85 g
INACTIVE INGREDIENTS: LANOLIN; CARNAUBA WAX; LANOLIN OIL; CITRAL; .BETA.-CITRONELLOL, (R)-; GERANIOL; LINALOOL, (+/-)-; FERROSOFERRIC OXIDE; TITANIUM DIOXIDE; FD&C YELLOW NO. 5; FD&C YELLOW NO. 6

Drug Facts

Active Ingredient

Petrolatum 85%

Purpose

Skin Protectant

Uses

- Temporarily protects and helps relieve
- chapping
- peeling or flaking due to minor sunburn
- windburn
- cracked lips

Directions

- Apply liberally as often as necessary

Inactive Ingredients

LANOLIN, COPERNICIA CERIFERA (CARNAUBA) WAX/CERA CARNAUBA/CIRE DE CARNAUBA, BIS-DIGLYCERYL POLYACYLADIPATE-2, LANOLIN OIL, PARFUM/FRAGRANCE, CITRAL, CITRONELLOL, GERANIOL, LIMONENE, LINALOOL, IRON OXIDES (CI 77499), TITANIUM DIOXIDE (CI 77891), YELLOW 5 LAKE (CI 19140), YELLOW 6 LAKE (CI 15985).

Questions or comments?

Call toll free 1-800 326-7337

Principal Display Panel - Eight Hour Lip Protectant Carton Label

ElizabethArden

NEW YORK

AROUND
WITH 8 HOUR
THE WORLD

Take Off
and Touch Down

Lip Duo

Lip Scrub

Lip Protectant

NET WT. .45 OZ. 13g EACH